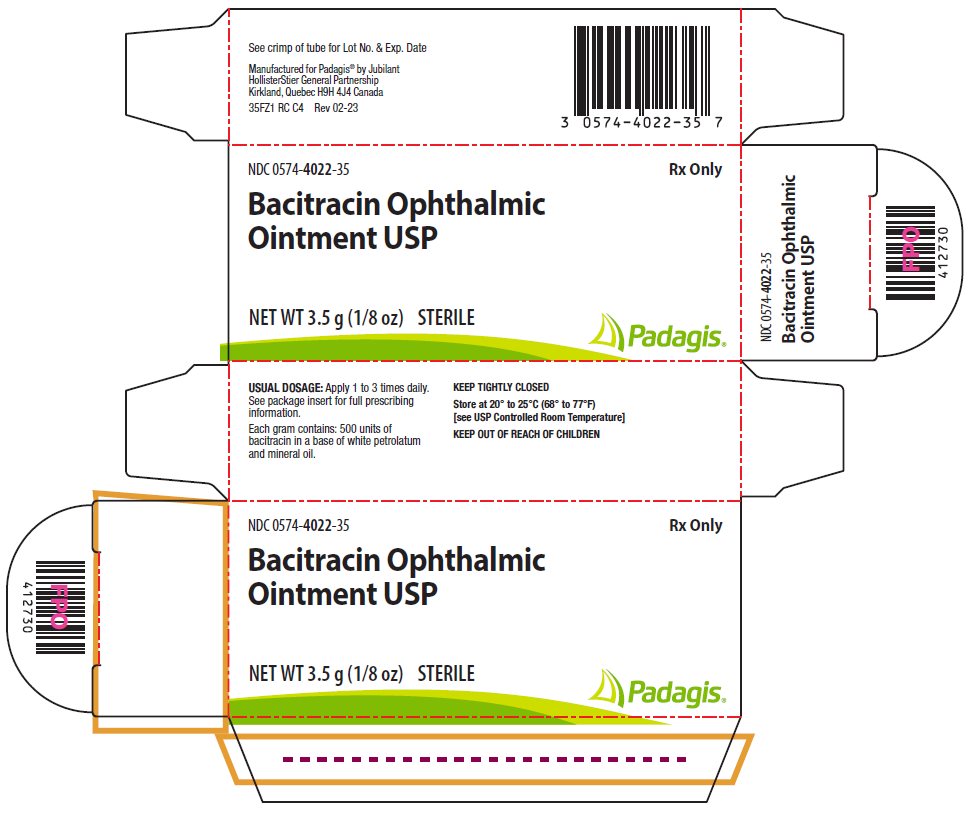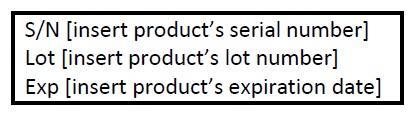 DRUG LABEL: Bacitracin
NDC: 0574-4022 | Form: OINTMENT
Manufacturer: Padagis US LLC
Category: prescription | Type: HUMAN PRESCRIPTION DRUG LABEL
Date: 20241031

ACTIVE INGREDIENTS: BACITRACIN 500 [USP'U]/1 g
INACTIVE INGREDIENTS: PETROLATUM; MINERAL OIL

Bacitracin Ophthalmic Ointment USP

DESCRIPTION:

Each gram of ointment contains 500 units of Bacitracin in a low melting special base containing White Petrolatum and Mineral Oil.

CLINICAL PHARMACOLOGY:

The antibiotic, Bacitracin, exerts a profound action against many gram-positive pathogens, including the common Streptococci and Staphylococci. It is also destructive for certain gram-negative organisms. It is ineffective against fungi.

INDICATIONS AND USAGE:

For the treatment of superficial ocular infections involving the conjunctiva and/or cornea caused by Bacitracin susceptible organisms.

CONTRAINDICATIONS:

This product should not be used in patients with a history of hypersensitivity to Bacitracin.

PRECAUTIONS:

Bacitracin ophthalmic ointment should not be used in deep-seated ocular infections or in those that are likely to become systemic. The prolonged use of antibiotic containing preparations may result in overgrowth of nonsusceptible organisms particularly fungi. If new infections develop during treatment appropriate antibiotic or chemotherapy should be instituted.

ADVERSE REACTIONS:

Bacitracin has such a low incidence of allergenicity that for all practical purposes side reactions are practically non-existent. However, if such reaction should occur, therapy should be discontinued.

To report SUSPECTED ADVERSE REACTIONS, contact Padagis® at 1-866-634-9120 or FDA at 1-800-FDA-1088 or www.fda.gov/medwatch.

DOSAGE AND ADMINISTRATION:

The ointment should be applied directly into the conjunctival sac 1 to 3 times daily. In blepharitis all scales and crusts should be carefully removed and the ointment then spread uniformly over the lid margins. Patients should be instructed to take appropriate measures to avoid gross contamination of the ointment when applying the ointment directly to the infected eye.

HOW SUPPLIED:

NDC 0574-4022-35 3.5 g (1/8 oz.) sterile tamper evident tubes with ophthalmic tip.

Store at 20°-25°C (68°-77°F) [see USP Controlled Room Temperature].

Manufactured for Padagis® by Jubilant HollisterStier General Partnership
Kirkland, Quebec H9H 4J4 Canada

35F00 RC PH2
Rev 02-23

PACKAGE/LABEL PRINCIPAL DISPLAY PANEL – 3.5 g Carton

NDC 0574-4022-35

Rx Only

Bacitracin Ophthalmic Ointment USP

NET WT 3.5 g (1/8 oz)

STERILE

The following image is a placeholder representing the product identifier that is either affixed or imprinted on the drug package label during the packaging operation.